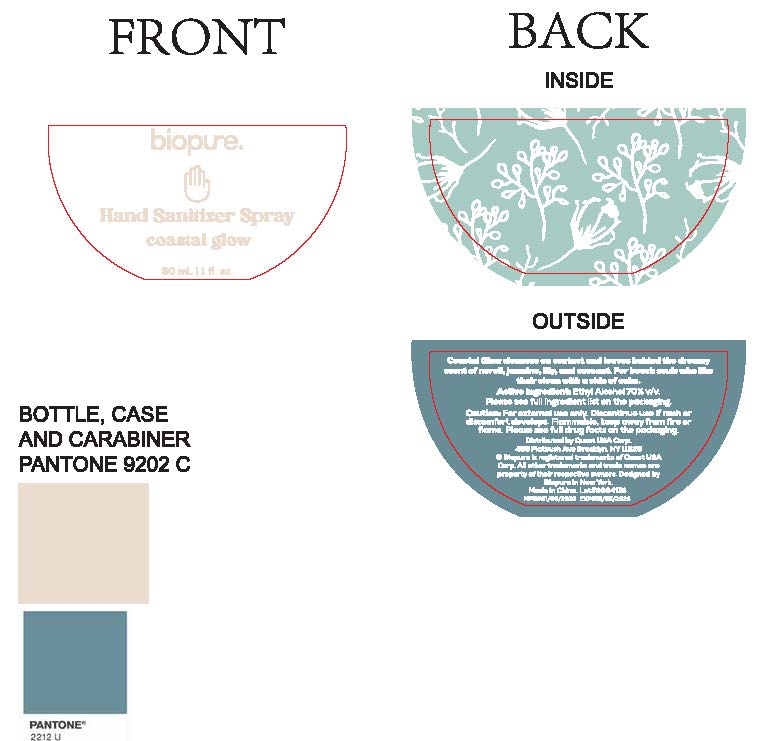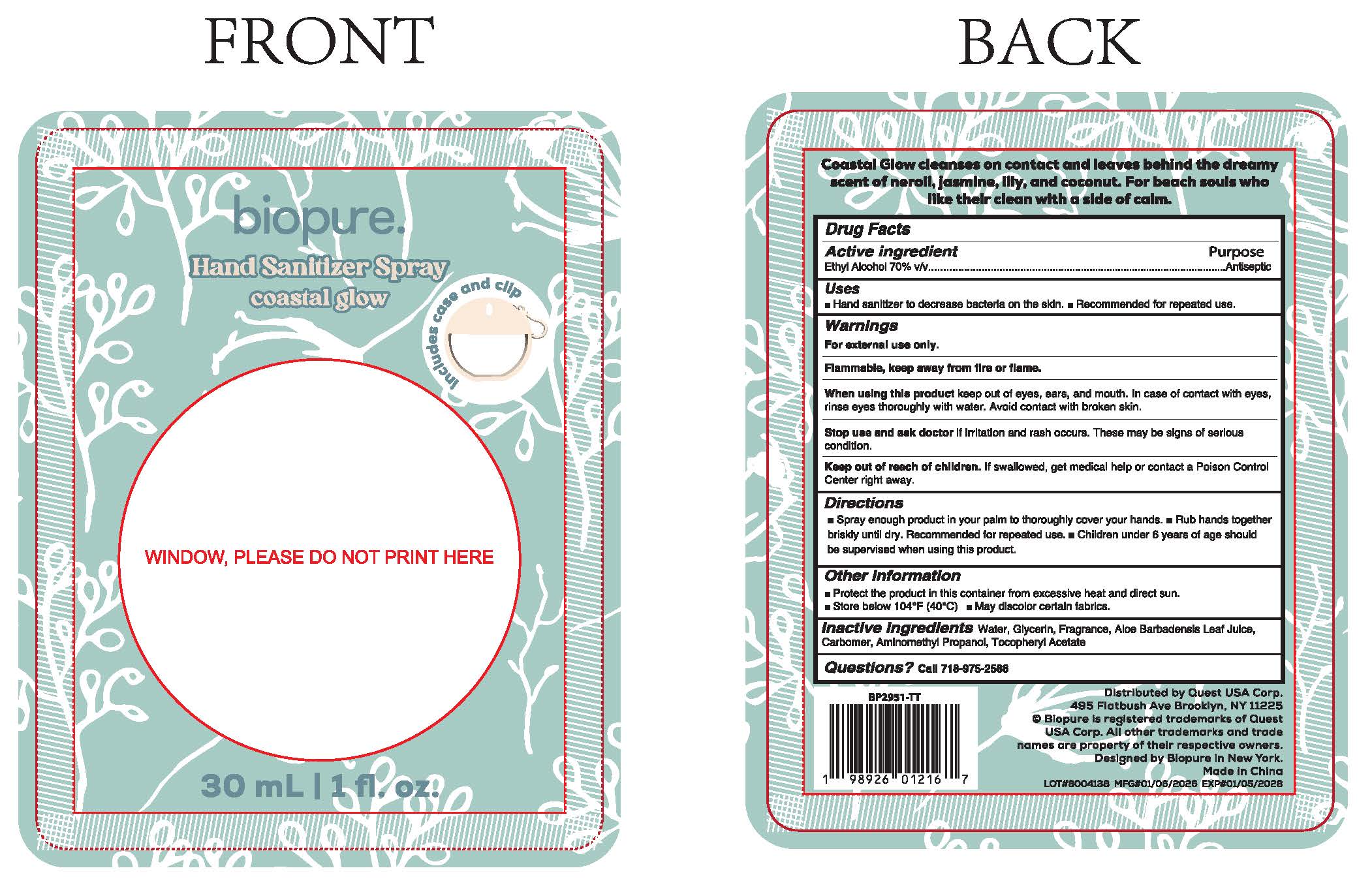 DRUG LABEL: BIOPURE Hand Sanitizer Spray-Coastal Glow
NDC: 78691-037 | Form: LIQUID
Manufacturer: Quest USA Corp
Category: otc | Type: HUMAN OTC DRUG LABEL
Date: 20260115

ACTIVE INGREDIENTS: ALCOHOL 16 g/30 mL
INACTIVE INGREDIENTS: AMINOMETHYL PROPANOL; WATER; ALOE BARBADENSIS LEAF; GLYCERIN; CARBOMER; ALPHA-TOCOPHEROL ACETATE

BIOPURE HAND SANITIZER SPRAY-Coastal Glow

Active Ingredient(s)

Ethyl Alcohol 70% v/v

Purpose

Antiseptic

Use

- Hand sanitizer to decrease bacteria on the skin.
- Recommended for repeated use.

Warnings

For external use only.

Flammable, keep away from fire or flame.

Do not use

Stop use and ask doctor
if irritation and rash occurs. These may be signs of serious condition.

When using this product
keep out of eyes, ears and mouth. In case of contact with eyes, rinse eyes thoroughly with water. Avoid contact with broken skin.

Stop use and ask doctorif irritation and rash occurs. These may be signs of serious condition.

Keep out of reach of children.If swallowed, get medical help or contact a Poison Control Center right away.

Directions

●Spray enough product in your palm to thoroughly cover your hands.

●Rub hands together briskly until dry. Recommended for repeated use.

●Children under 6 years of age should be supervised by an adult when using this product.

Other information

● Protect the product in this container from excessive heat and direct sun.
● Store below 104°F (40°C).

● May discolor certain fabrics.

Inactive ingredients

Water, Glycerin, Fragrance, Aloe Barbadensis Leaf Juice, Carbomer, Aminoethyl Propanol, Tocoheryl Acetate

Questions

Questions? call 718-975-2586